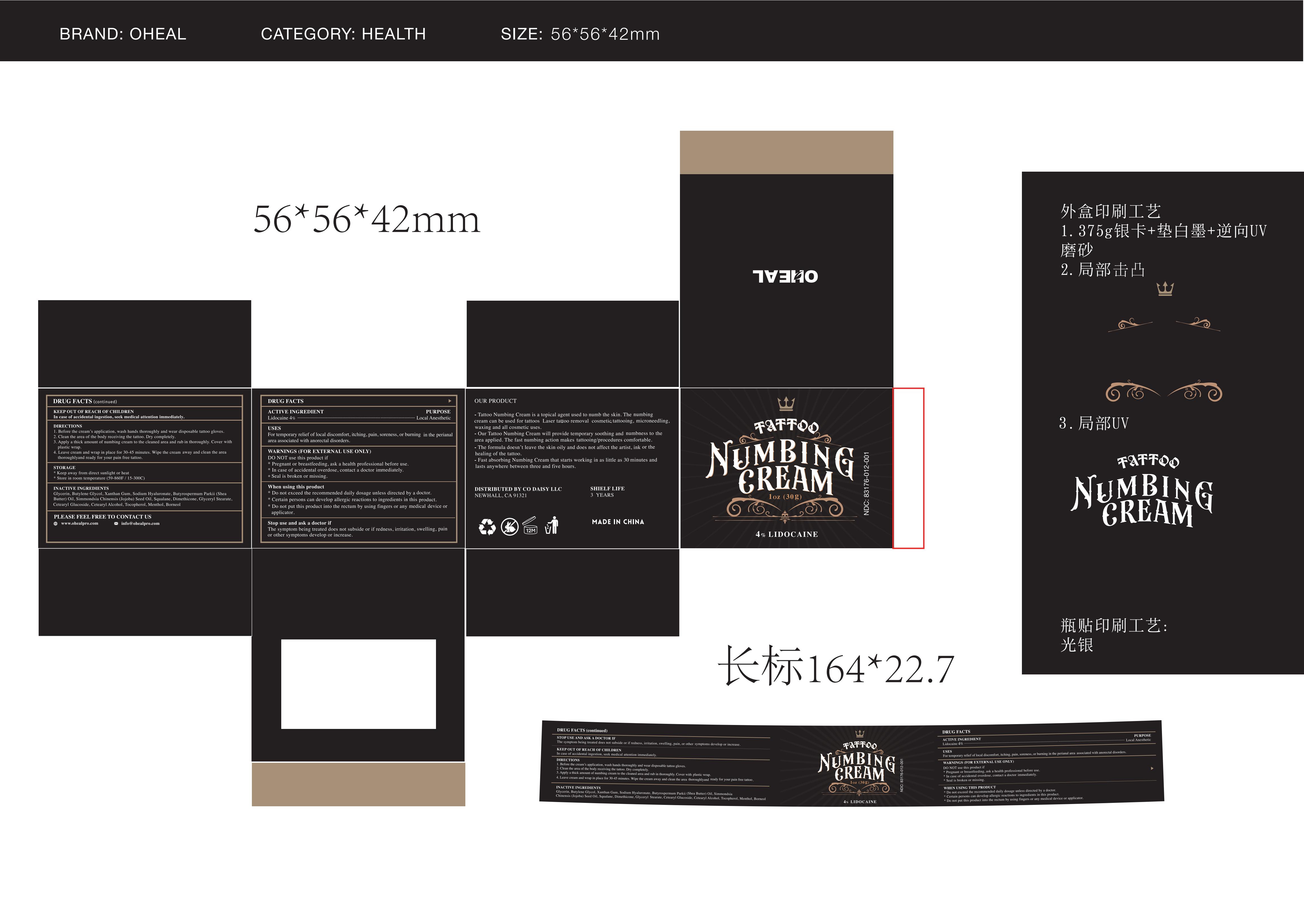 DRUG LABEL: Oheal Tattoo Numbing Cream
NDC: 84746-005 | Form: CREAM
Manufacturer: Shandong Yuyaotang Pharmaceutical Co., Ltd
Category: otc | Type: HUMAN OTC DRUG LABEL
Date: 20241212

ACTIVE INGREDIENTS: LIDOCAINE 4 g/100 mL
INACTIVE INGREDIENTS: BUTYLENE GLYCOL; XANTHAN GUM; HYALURONATE SODIUM; GLYCERYL 1-STEARATE; BORNEOL; CETEARYL GLUCOSIDE; TOCOPHEROL; MENTHOL; BUTYROSPERMUM PARKII (SHEA) BUTTER UNSAPONIFIABLES; JOJOBA OIL; CETOSTEARYL ALCOHOL; SQUALANE; GLYCERIN; DIMETHICONE

84746-005 COMPLETED

Active Ingredient

Lidocaine 4%

Purpose

Local Anesthetic

Use

For temporary relief of local discomfort, itching, pain, soreness, or burning in the perianal
area associated with anorectal disorders.

Warnings

For External Use Only
●Pregnant or breastfeeding, ask a health professional before use.
●In case of accidental overdose, contact a doctor or Poison Control Center immediately.
●Seal is broken or missing.

Do not use

●Pregnant or breastfeeding, ask a health professional before use.
●In case of accidental overdose, contact a doctor or Poison Control Center immediately.
●Seal is broken or missing.

When Using

●Do not exceed the recommended daily dosage unless directed by a doctor.
●Certain persons can develop allergic reactions to ingredients in this product.
●Do not put this product into the rectum by using fingers or any medical device or applicator.

Stop Use

The symptom being treated does not subside or if redness, irritation, swelling, pain, or other symptoms develop or increase.

Ask Doctor

The symptom being treated does not subside or if redness, irritation, swelling, pain, or other symptoms develop or increase.

Keep Oot Of Reach Of Children

In case of accidental ingestion, seek medical attention immediately.

Directions

1. Before the cream’s application, wash hands thoroughly and wear disposable tattoo gloves.
2. Clean the area of the body receiving the tattoo. Dry completely.
3. Apply a thick amount of numbing cream to the cleaned area and rub in thoroughly, Cover with plastic wrap.
4. Leave cream and wrap in place for 30-45 minutes. Wipe the cream away and clean the area thoroughly, ready for your pain free tattoo.

Other information

●Keep away from direct sunlight or heat
●Store in room temperature (59-860F / 15-300C)

Inactive ingredients

Glycerin, Butylene Glycol, Xanthan Gum, Sodium Hyaluronate, Butyrospermum Parkii (Shea Butter) Oil, Simmondsia Chinensis (Jojoba) Seed Oil, Squalane, Dimethicone, Glyceryl Stearate, Cetearyl Glucoside, Cetearyl Alcohol, Tocopherol, Menthol, Borneol

Questions

www.ohealpro.com

Info@ohealpro.com
669-588-4076